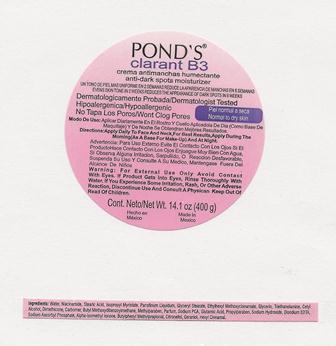 DRUG LABEL: Ponds Clarant B3
NDC: 69772-615 | Form: CREAM
Manufacturer: Teresa Cecena DBA Genesis
Category: otc | Type: HUMAN OTC DRUG LABEL
Date: 20150526

ACTIVE INGREDIENTS: AVOBENZONE 100 g/3 g
INACTIVE INGREDIENTS: SODIUM HYDROXIDE; TROLAMINE; GLUTAMIC ACID; EDETATE DISODIUM; SODIUM ASCORBYL PHOSPHATE; .BETA.-CITRONELLOL, (R)-; .ALPHA.-HEXYLCINNAMALDEHYDE; NIACINAMIDE; ISOPROPYL MYRISTATE; PROPYLPARABEN; GERANIOL; BUTYLPHENYL METHYLPROPIONAL; ISOMETHYL-.ALPHA.-IONONE; WATER; STEARIC ACID; MINERAL OIL; GLYCERYL MONOSTEARATE; OCTINOXATE; GLYCERIN; CETOSTEARYL ALCOHOL; DIMETHICONE; METHYLPARABEN; SODIUM PYRROLIDONE CARBOXYLATE

ACTIVE INGREDIENT

AVOBENZONE

INACTIVE INGREDIENT

Water, myristic acid,stearic acid,niacinamide,ethylhexyl methoxycinnamate,glycerin, tapioca starch, triethanolamine, cyclopentasiloxane,PEG/PPG-18/18 dimethocone, cetyl alcohol, butyl methpxydibenzoylmethane, phnpxyethanol,fragance, carbomer, acrylates crosspolymer, methylparabene,propylparabene, disodium EDTA, sodium ascorbyl phosphate.

WARNINGS

FOR EXTERNAL USE ONLY.

AVOID CONTACT WITH EYES. If product gets into eyes, rinse thoroughly with water.

Discontinue use and consult a physican:

If you experience some irritation rash or other adverse reaction

DOSAGE AND ADMINISTRATION

Apply daily to face and ne ck. For best results, apply during the morning (as a base for your make-up) and night.